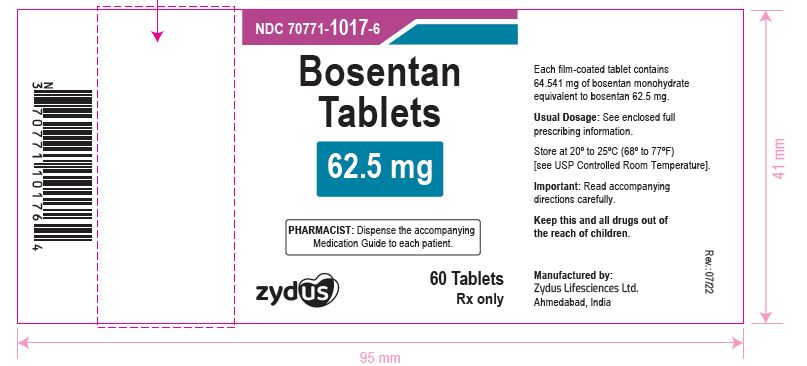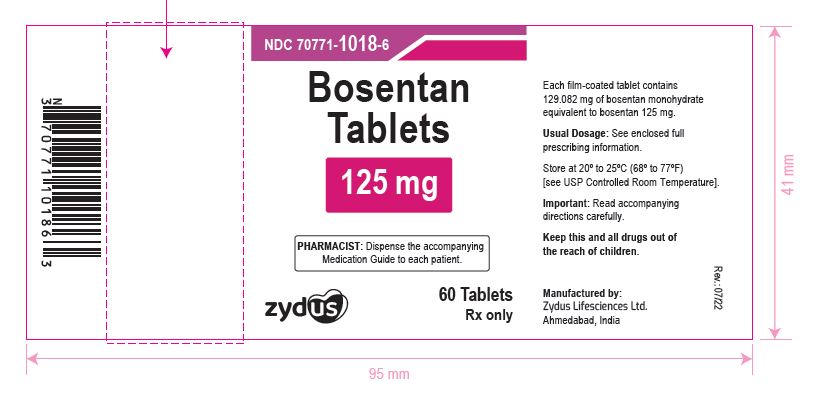 DRUG LABEL: Bosentan
NDC: 70771-1017 | Form: TABLET
Manufacturer: Zydus Lifesciences Limited
Category: prescription | Type: HUMAN PRESCRIPTION DRUG LABEL
Date: 20241125

ACTIVE INGREDIENTS: BOSENTAN 62.5 mg/1 1
INACTIVE INGREDIENTS: ETHYLCELLULOSE, UNSPECIFIED; FERRIC OXIDE RED; FERRIC OXIDE YELLOW; GLYCERYL DIBEHENATE; HYPROMELLOSE, UNSPECIFIED; MAGNESIUM STEARATE; POVIDONE; SODIUM STARCH GLYCOLATE TYPE A POTATO; STARCH, CORN; TALC; TITANIUM DIOXIDE; TRIACETIN

BOSENTAN TABLETS

PACKAGE LABEL.PRINCIPAL DISPLAY PANEL

NDC 70771-1017-6

Bosentan tablets, 62.5 mg

60 tablets

Rx only

NDC 70771-1018-6

Bosentan tablets, 125 mg

60 tablets

Rx only